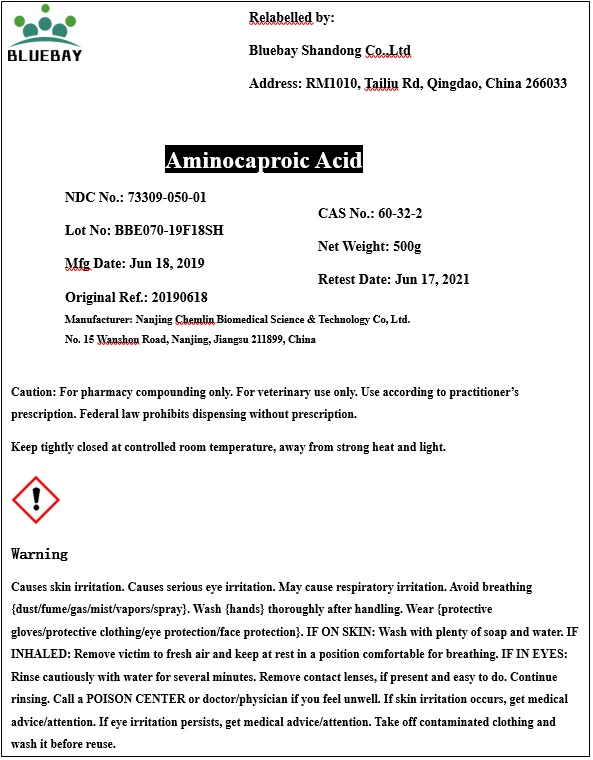 DRUG LABEL: Aminocaproic Acid
NDC: 73309-050 | Form: POWDER
Manufacturer: BLUEBAY SHANDONG CO.,LTD
Category: other | Type: BULK INGREDIENT
Date: 20191031

ACTIVE INGREDIENTS: AMINOCAPROIC ACID 1 g/1 g

Aminocaproic Acid